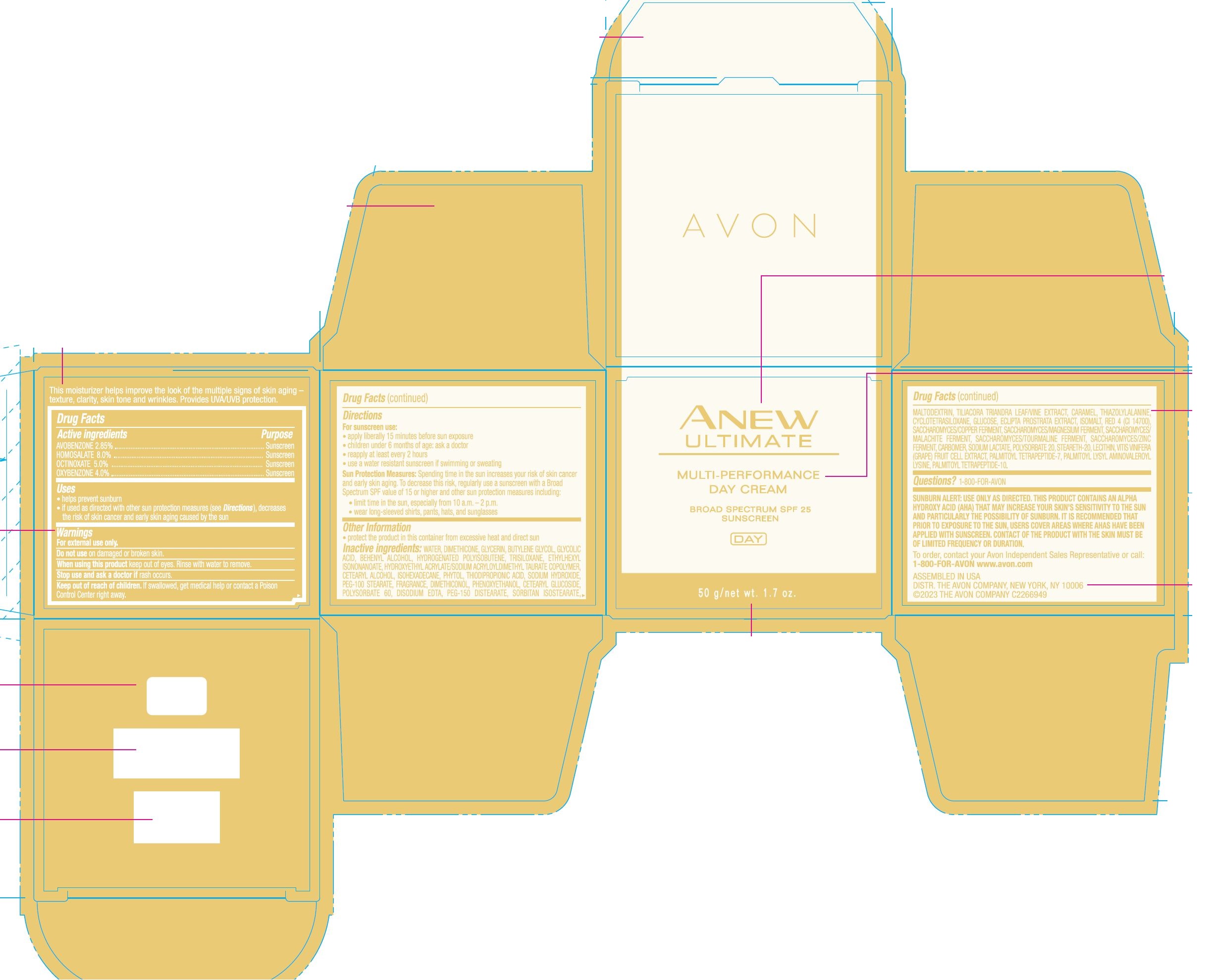 DRUG LABEL: Avon Anew Ultimate Day Multi-Performance-Cream SPF 25 Sunscreen
NDC: 10096-2650 | Form: CREAM
Manufacturer: The Avon Company
Category: otc | Type: HUMAN OTC DRUG LABEL
Date: 20240103

ACTIVE INGREDIENTS: OCTINOXATE 5 mg/1 g; HOMOSALATE 8 mg/1 g; OXYBENZONE 4 mg/1 g; AVOBENZONE 2.85 mg/1 g
INACTIVE INGREDIENTS: WATER

Avon Anew Ultimate Day Multi-Performance Cream SPF 25 50g

Drug Facts

AVOBENZONE 2.85%
HOMOSALATE 8.0%
OCTINOXATE 5.0%
OXYBENZONE 4.0%

Purpose

Sunscreen

Uses

- helps prevent sunburn
- if used as directed with other sun protection measures (see Directions), decrease the rist of skin cancer and early skin aging caused by the sun

Warnings

For external use only.

Do not use on damaged or broken skin.

When using this product keep out of eyes. Rinse with water to remove.

Stop use and ask a doctor if rash occurs.

Keep out of reach of children. If swallowed, get medical help or contact a Poison Control Center right away.

Directions

For sunscreen use:

- apply liberally 15 minutes before sun exposure
- children less than 6 months of age: ask a doctor
- reapply at least every 2 hours
- use a water resistant sunscreen if swimming or sweating

Sun Protection Measures: Spending time in the sun increases your risk of skin cancer and early skin aging. To decrease this risk, regularly use a sunscreen with a Broad Spectrum SPF value of 15 or higher and other sun protection measures including:

- limit time in the sun, especially from 10 a.m. – 2 p.m.
- wear long-sleeved shirts, pants, hats, and sunglasses

Other Information

• protect the product in this container from excessive heat and direct sun

Inactive Ingredients:

WATER, DIMETHICONE, GLYCERIN, BUTYLENE GLYCOL, GLYCOLIC ACID, BEHENYL ALCOHOL, HYDROGENATED POLYISOBUTENE, TRISILOXANE, ETHYLHEXYL ISONONANOATE, HYDROXYETHYL ACRYLATE/SODIUM ACRYLOYLDIMETHYL TAURATE COPOLYMER, CETEARYL ALCOHOL, ISOHEXADECANE, PHYTOL, THIODIPROPIONIC ACID, SODIUM HYDROXIDE, PEG-100 STEARATE, FRAGRANCE, DIMETHICONOL, PHENOXYETHANOL, CETEARYL GLUCOSIDE, POLYSORBATE 60, DISODIUM EDTA, PEG-150 DISTEARATE, SORBITAN ISOSTEARATE, MALTODEXTRIN, TILIACORA TRIANDRA LEAF/VINE EXTRACT, CARAMEL, THIAZOLYLALANINE, CYCLOTETRASILOXANE, GLUCOSE, ECLIPTA PROSTRATA EXTRACT, ISOMALT, RED 4 (CI 14700), SACCHAROMYCES/COPPER FERMENT, SACCHAROMYCES/MAGNESIUM FERMENT, SACCHAROMYCES/MALACHITE FERMENT, SACCHAROMYCES/TOURMALINE FERMENT, SACCHAROMYCES/ZINC FERMENT, CARBOMER, SODIUM LACTATE, POLYSORBATE 20, STEARETH-20, LECITHIN, VITIS VINIFERA (GRAPE) FRUIT CELL EXTRACT, PALMITOYL TETRAPEPTIDE-7, PALMITOYL LYSYL AMINOVALEROYL LYSINE, PALMITOYL TETRAPEPTIDE-10

Questions?

1-800-FOR-AVON

Principal Display Panel:

AVON
ANEW
ULTIMATE
MULTI-PERFORMANCE
DAY CREAM
BROAD SPECTRUM SPF 25
SUNSCREEN
DAY
50 g / net wt. 1.7 oz.
This moisturizer helps improve the look of the multiple signs of skin aging -
texture, clarity, skin tone and wrinkles. Provides UVA/UVB protection.
To order, contact your Avon Independent Sales Representative or call:
1-800-FOR-AVON www.avon.com
ASSEMBLED IN USA
DISTR. THE AVON COMPANY, NEW YORK, NY 10006
©2023 THE AVON COMPANY C2266949